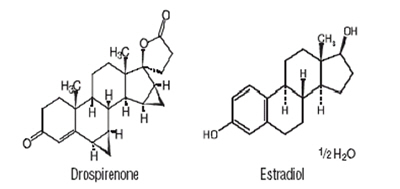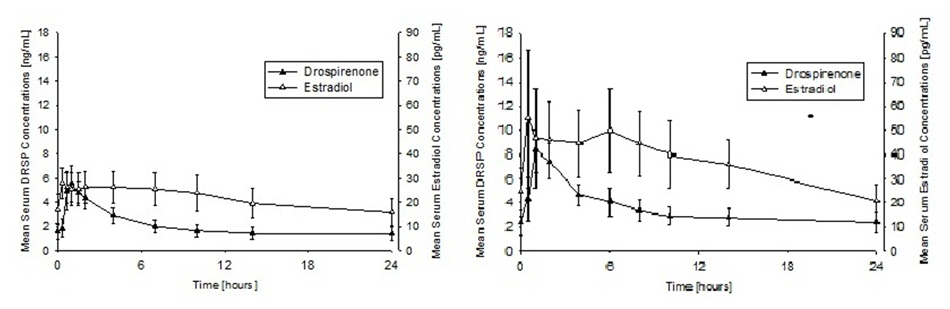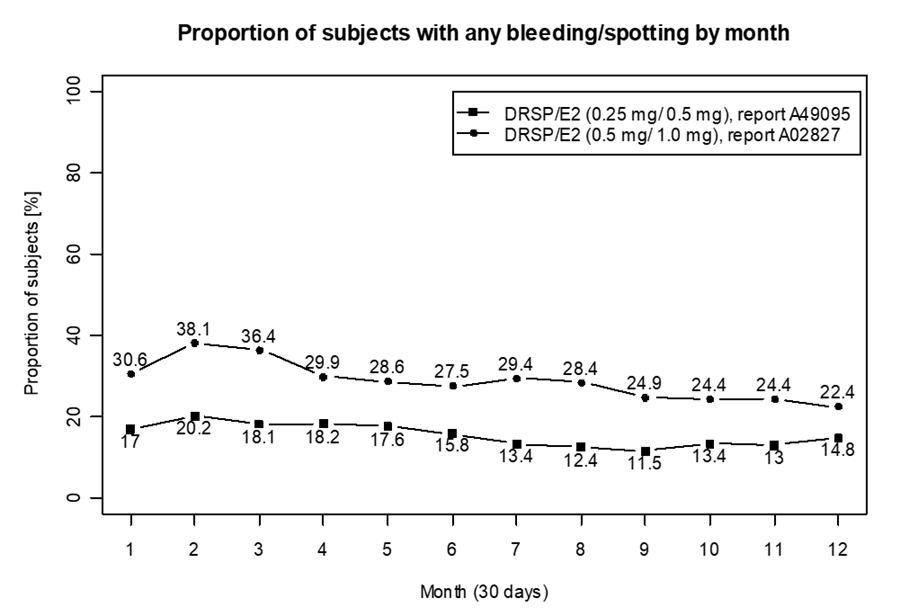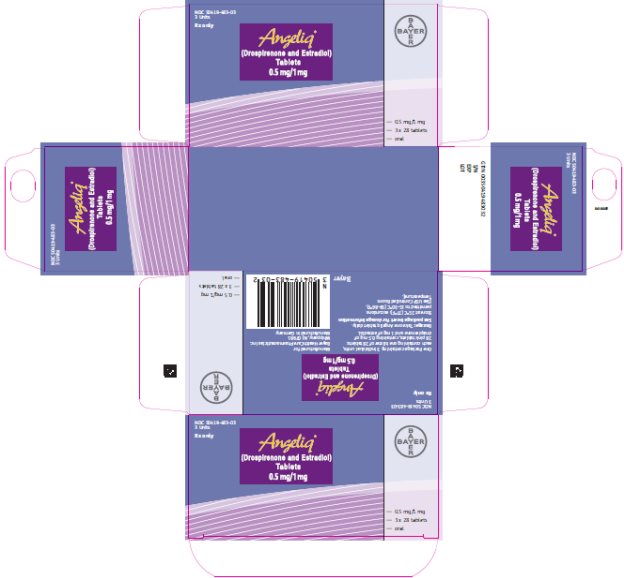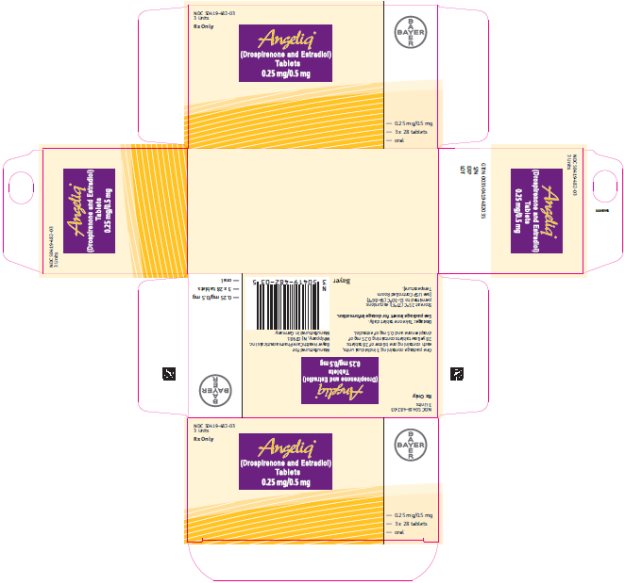 DRUG LABEL: Angeliq
NDC: 50419-483 | Form: TABLET, FILM COATED
Manufacturer: Bayer HealthCare Pharmaceuticals Inc.
Category: prescription | Type: HUMAN PRESCRIPTION DRUG LABEL
Date: 20260302

ACTIVE INGREDIENTS: ESTRADIOL 1 mg/1 1; DROSPIRENONE 0.5 mg/1 1
INACTIVE INGREDIENTS: STARCH, CORN; FERRIC OXIDE RED; HYPROMELLOSE, UNSPECIFIED; LACTOSE MONOHYDRATE; POLYETHYLENE GLYCOL 6000; MAGNESIUM STEARATE; POVIDONE K25; TALC; TITANIUM DIOXIDE

HIGHLIGHTS OF PRESCRIBING INFORMATION

These highlights do not include all the information needed to use ANGELIQ safely and effectively. See full prescribing information for ANGELIQ.
ANGELIQ (drospirenone and estradiol) tablets, for oral use
Initial U.S. Approval: 2005

WARNING: CARDIOVASCULAR DISORDERS, PROBABLE DEMENTIA, BREAST CANCER, and ENDOMETRIAL CANCER

WARNING: CARDIOVASCULAR DISORDERS, PROBABLE DEMENTIS, BREAST CANCER, and ENDOMETRIAL CANCER

See full prescribing information for complete boxed warning

Estrogen Plus Progestin Therapy

- The Women's Health Initiative (WHI) estrogen plus progestin substudy reported increased risks of pulmonary embolism (PE), deep vein thrombosis (DVT), stroke, and myocardial infarction (MI) (5.1)
- The WHI estrogen plus progestin substudy reported increased risks of invasive breast cancer (5.2)
- The WHI Memory Study (WHIMS) estrogen plus progestin ancillary study of WHI reported an increased risk of probable dementia in postmenopausal women 65 years of age and older (5.4)
- Do not use estrogen plus progestogen therapy for the prevention of cardiovascular disease or dementia (5.1, 5.4)

Estrogen-Alone Therapy

- There is an increased risk of endometrial cancer in a woman with a uterus who uses unopposed estrogens (5.3)
- The WHI estrogen-alone substudy reported increased risks of stroke and DVT (5.1)
- The WHIMS estrogen-alone ancillary study of WHI reported an increased risk of probable dementia in postmenopausal women 65 years of age and older (5.4)
- Do not use estrogen-alone therapy for the prevention of cardiovascular disease or dementia (5.1, 5.4)

RECENT MAJOR CHANGES

Boxed Warning | 10/2023
Warnings and Precautions (5.3) | 12/2023

1 INDICATIONS AND USAGE

Angeliq is a combination of an estrogen and progestin indicated in a woman with a uterus for the treatment of:

- Moderate to severe vasomotor symptoms due to menopause. (1.1)
- Moderate to severe vulvar and vaginal atrophy symptoms due to menopause. (1.2)
  Limitation of Use
  When prescribing solely for the treatment of moderate to severe symptoms of vulvar and vaginal atrophy, first consider the use of topical vaginal products.

2 DOSAGE AND ADMINISTRATION

- Start therapy with Angeliq 0.25 mg drospirenone (DRSP)/0.5 mg estradiol (E2) once daily for the treatment of moderate to severe vasomotor symptoms due to menopause. Dosage adjustment should be guided by the clinical response (2.1)
- Start therapy with Angeliq 0.5 mg DRSP/1 mg E2 once daily for the treatment of moderate to severe vulvar and vaginal atrophy due to menopause (2.2)

3 DOSAGE FORMS AND STRENGTHS

- Tablet: 0.25 mg DRSP/0.5 mg E2 and 0.5 mg DRSP/1 mg E2 (3)

4 CONTRAINDICATIONS

- Undiagnosed abnormal genital bleeding (4, 5.3)
- Breast cancer or a history of breast cancer (4, 5.3)
- Estrogen-dependent neoplasia (4, 5.3)
- Active DVT, PE, or a history of these conditions (4, 5.1)
- Active arterial thromboembolic disease (for example, stroke and MI), or history of these conditions (4, 5.1)
- Renal impairment (4, 5.2)
- Hepatic impairment or disease (4, 5.2)
- Adrenal insufficiency (4, 5.2)
- Protein C, protein S, or antithrombin deficiency, or other known thrombophilic disorders (4)
- Known anaphylactic reaction, angioedema, or hypersensitivity to Angeliq (4, 5.16)

5 WARNINGS AND PRECAUTIONS

- Do not use with conditions that predispose to hyperkalemia (5.2
- Estrogens increase the risk of gallbladder disease (5.5)
- Discontinue estrogen if severe hypercalcemia, loss of vision, severe hypertriglyceridemia or cholestatic jaundice occurs (5.6, 5.7, 5.9, 5.10)
- Monitor thyroid function in women on thyroid hormone replacement therapy (5.11, 5.19)

6 ADVERSE REACTIONS

The most common adverse reactions with Angeliq that occurred in at least 1% of users in clinical trials are: gastrointestinal and abdominal pain, female genital tract bleeding, breast pain and discomfort, and headache. (6.1)

To report SUSPECTED ADVERSE REACTIONS, contact Bayer HealthCare Pharmaceuticals Inc. at 1-888-842-2937 or FDA at 1-800-FDA-1088 or www.fda.gov/medwatch

7 DRUG INTERACTIONS

- Inducers and inhibitors of CYP3A4 may affect estrogen drug metabolism and decrease or increase the estrogen plasma concentration. (7.1)
- Serum potassium concentration may increase in women taking drospirenone with other drugs that have the potential to increase potassium. (7.1)

FULL PRESCRIBING INFORMATION

WARNING: CARDIOVASCULAR DISORDERS, PROBABLE DEMENTIA, BREAST CANCER, and ENDOMETRIAL CANCER

Estrogen Plus Progestin Therapy

Cardiovascular Disorders and Probable Dementia

The Women's Health Initiative (WHI) estrogen plus progestin substudy reported increased risks of pulmonary embolism (PE), deep vein thrombosis (DVT), stroke, and myocardial infarction (MI) in postmenopausal women (50 to 79 years of age) during 5.6 years of treatment with daily oral conjugated estrogens (CE) [0.625 mg] combined with medroxyprogesterone acetate (MPA) [2.5 mg], relative to placebo [see Warnings and Precautions (5.1), and Clinical Studies (14.5)].

The WHI Memory Study (WHIMS) estrogen plus progestin ancillary study of WHI reported an increased risk of developing probable dementia in postmenopausal women 65 years of age and older during 4 years of treatment with daily CE (0.625 mg) combined with MPA (2.5 mg), relative to placebo. It is unknown whether this finding applies to younger postmenopausal women [see Warnings and Precautions (5.4), Use in Specific Populations (8.5), and Clinical Studies (14.5)].

Do not use estrogen plus progestogen therapy for the prevention of cardiovascular disease or dementia [see Warnings and Precautions (5.1, 5.4), Clinical Studies (14.4, 14.5)].

Breast Cancer

The WHI estrogen plus progestin substudy demonstrated an increased risk of invasive breast cancer [see Warnings and Precautions (5.3), and Clinical Studies (14.4)].

Only daily oral 0.625 mg CE and 2.5 mg MPA were studied in the estrogen plus progestin substudy of WHI. Therefore, the relevance of the WHI findings regarding adverse cardiovascular events, dementia and breast cancer to lower CE plus other MPA doses, other routes of administration, or other estrogen plus progestin products is not known. Without such data, it is not possible to definitively exclude these risks or determine the extent of these risks for other products. Discuss with your patient the benefits and risks of estrogen plus progestin therapy, taking into account her individual risk profile.

Prescribe estrogens with or without progestogens at the lowest effective doses and for the shortest duration consistent with treatment goals and risks for the individual woman.

Estrogen-Alone Therapy

Endometrial Cancer

There is an increased risk of endometrial cancer in a woman with a uterus who uses unopposed estrogens. Adding a progestogen to estrogen therapy has been shown to reduce the risk of endometrial hyperplasia, which may be a precursor to endometrial cancer. Perform adequate diagnostic measures, including directed or random endometrial sampling when indicated, to rule out malignancy in postmenopausal women with undiagnosed persistent or recurring abnormal genital bleeding [see Warnings and Precautions (5.3)].

Cardiovascular Disorders and Probable Dementia

The WHI estrogen-alone substudy reported increased risks of stroke and DVT in postmenopausal women (50 to 79 years of age) during 7.1 years of treatment with daily oral CE (0.625 mg)-alone, relative to placebo [see Warnings and Precautions (5.1), and Clinical Studies (14.5)].

The WHIMS estrogen-alone ancillary study of WHI reported an increased risk of developing probable dementia in postmenopausal women 65 years of age and older during 5.2 years of treatment with daily CE (0.625 mg)-alone, relative to placebo. It is unknown whether this finding applies to younger postmenopausal women [see Warnings and Precautions (5.4), Use in Specific Populations (8.5), and Clinical Studies (14.5)].

Do not use estrogen-alone therapy for the prevention of cardiovascular disease or dementia [see Warnings and Precautions (5.1, 5.4) and Clinical Studies (14.4, 14.5)].

Only daily oral 0.625 mg CE was studied in the estrogen-alone substudy of the WHI. Therefore, the relevance of the WHI findings regarding adverse cardiovascular events and dementia to lower CE doses, other routes of administration, or other estrogen-alone products is not known. Without such data, it is not possible to definitively exclude these risks or determine the extent of these risks for other products. Discuss with your patient the benefits and risks of estrogen-alone therapy, taking into account her individual risk profile.

Prescribe estrogens with or without progestogens at the lowest effective doses and for the shortest duration consistent with treatment goals and risks for the individual woman.

1 INDICATIONS AND USAGE

Use estrogen, alone or in combination with a progestogen, at the lowest effective dose and the shortest duration consistent with treatment goals and risks for the individual woman. Re-evaluate postmenopausal women periodically as clinically appropriate to determine whether treatment is still necessary.

1.1 Treatment of Moderate to Severe Vasomotor Symptoms due to Menopause

- Angeliq 0.25 mg drospirenone (DRSP)/0.5 mg estradiol (E2) is indicated for the treatment of moderate to severe vasomotor symptoms due to menopause in a woman with a uterus.
- Angeliq 0.5 mg DRSP/1 mg E2 is indicated for the treatment of moderate to severe vasomotor symptoms associated due to menopause in a woman with a uterus.

1.2 Treatment of Moderate to Severe Symptoms of Vulvar and Vaginal Atrophy due to Menopause

- Angeliq 0.5 mg DRSP/1 mg E2 is indicated for the treatment of moderate to severe symptoms of vulvar and vaginal atrophy due to menopause in a woman with a uterus.

2 DOSAGE AND ADMINISTRATION

Each pack of Angeliq covers 28 days of treatment. Treatment is continuous, which means that the next pack follows immediately without a break. The tablets are to be swallowed whole with some liquid irrespective of food intake and should preferably be taken at the same time every day. In case a tablet is forgotten, it should be taken as soon as possible. If more than 24 hours have elapsed, the missed tablet should not be taken. If several tablets are forgotten, bleeding may occur.

Women who do not take estrogens or women who change from a continuous combination product may start treatment at any time. Women changing from a continuous sequential or cyclic hormone therapy (HT) should complete the current cycle of therapy before initiating Angeliq therapy.

2.1 Treatment of Moderate to Severe Vasomotor Symptoms due to Menopause

One Angeliq 0.25 mg DRSP/0.5 mg E2 tablet or one Angeliq 0.5 mg DRSP/1 mg E2 tablet taken by mouth once daily.

2.2 Treatment of Moderate to Severe Symptoms of Vulvar and Vaginal Atrophy due to Menopause

One Angeliq 0.5 mg DRSP/1 mg E2 tablet taken by mouth once daily.

Limitation of Use

When prescribing solely for the treatment of moderate to severe symptoms of vulvar and vaginal atrophy, first consider the use of topical vaginal products.

3 DOSAGE FORMS AND STRENGTHS

Angeliq 0.25 mg DRSP/0.5 mg E2 Tablets: round, biconvex, yellow, film-coated, embossed with a "EL" inside a hexagon

Angeliq 0.5 mg DRSP/1 mg E2 Tablets: round, biconvex, pink, film-coated, embossed with a "CK" inside a hexagon

4 CONTRAINDICATIONS

Angeliq is contraindicated in women with any of the following conditions:

- Undiagnosed abnormal genital bleeding [see Warnings and Precautions (5.3)].
- Breast cancer or a history of breast cancer [see Warnings and Precautions (5.3)].
- Estrogen-dependent neoplasia [see Warnings and Precautions (5.3)].
- Active DVT, PE or history of these conditions [see Warnings and Precautions (5.1)].
- Active arterial thromboembolic disease (for example, stroke and MI) or history of these conditions [see Warnings and Precautions (5.1)].
- Renal Impairment [see Warnings and Precautions (5.2), Use in Specific Populations (8.7) and Clinical Pharmacology (12.3)].
- Hepatic impairment or disease [see Warnings and Precautions (5.10), Use in Specific Populations (8.6) and Clinical Pharmacology (12.3)].
- Adrenal insufficiency [see Warnings and Precautions (5.2)].
- Protein C, protein S, or antithrombin deficiency, or other known thrombophilic disorders
- Known anaphylactic reaction, angioedema, or hypersensitivity to Angeliq or any of its ingredients [see Adverse Reactions (6.2)]

5 WARNINGS AND PRECAUTIONS

5.1 Cardiovascular Disorders

Increased risks of PE, DVT, stroke, and MI are reported with estrogen plus progestin therapy. Increased risks of stroke and DVT are reported with estrogen-alone therapy. Immediately discontinue estrogen with or without progestogen therapy if any of these occur or are suspected.

Manage appropriately any risk factors for arterial vascular disease (for example, hypertension, diabetes mellitus, tobacco use, hypercholesterolemia, and/or obesity) and/or venous thromboembolism (VTE) [for example, personal history or family history of VTE, obesity, systemic lupus erythematosus].

Stroke

The WHI estrogen plus progestin substudy reported a statistically significant increased risk of stroke in women 50 to 79 years of age receiving daily CE (0.625 mg) plus MPA (2.5 mg) compared to women in the same age group receiving placebo (33 versus 25 strokes per 10,000 women years, respectively) [see Clinical Studies (14.4)]. The increase in risk was demonstrated after the first year and persisted.^1 Immediately discontinue estrogen with or without progestogen therapy if a stroke occurs or is suspected.

The WHI estrogen-alone substudy reported a statistically significant increased risk of stroke in women 50 to 79 years of age receiving daily CE (0.625 mg)-alone compared to women in the same age group receiving placebo (45 versus 33 strokes per 10,000 women-years). The increase in risk was demonstrated in year one and persisted ^1 [see Clinical Studies (14.4)]. Immediately discontinue estrogen-alone therapy if a stroke occurs or is suspected.

Subgroup analyses of women 50 to 59 years of age suggest no increased risk of stroke for those women receiving CE (0.625 mg)-alone versus those receiving placebo (18 versus 21 per 10,000 women-years).^1

Coronary Heart Disease

The WHI estrogen plus progestin substudy reported an increased risk (not statistically significant) of coronary heart disease (CHD) events (defined as nonfatal MI, silent MI, or CHD death) in those women receiving daily CE (0.625 mg) plus MPA (2.5 mg) compared to women receiving placebo (41 versus 34 per 10,000 women-years).^1 An increase in relative risk was demonstrated in year 1, and a trend toward decreasing relative risk was reported in years 2 through 5 [see Clinical Studies (14.4)].

The WHI estrogen-alone substudy reported no overall effect on CHD events in women receiving estrogen-alone compared to placebo^2 [see Clinical Studies (14.4)].

Subgroup analyses of women 50 to 59 years of age, who were less than 10 years since menopause, suggest a reduction (not statistically significant) in CHD events in those women receiving daily CE (0.625 mg)-alone compared to placebo (8 versus 16 per 10,000 women-years).^1

In postmenopausal women with documented heart disease (n=2,763), average 66.7 years of age, in a controlled clinical trial of secondary prevention of cardiovascular disease (Heart and Estrogen/Progestin Replacement Study; HERS), treatment with daily CE (0.625 mg) plus MPA (2.5 mg) demonstrated no cardiovascular benefit. During an average follow-up of 4.1 years, treatment with CE plus MPA did not reduce the overall rate of CHD events in postmenopausal women with established CHD. There were more CHD events in the CE plus MPA-treated group than in the placebo group in year 1, but not during the subsequent years. Two thousand, three hundred and twenty-one (2,321) women from the original HERS trial agreed to participate in an open label extension of HERS, HERS II. Average follow-up in HERS II was an additional 2.7 years, for a total of 6.8 years overall. Rates of CHD events were comparable among women in the CE plus MPA group and the placebo group in HERS, HERS II, and overall.

Venous Thromboembolism

The WHI estrogen plus progestin substudy reported a statistically significant 2-fold greater rate of VTE (DVT and PE) in women receiving daily CE (0.625 mg) plus MPA (2.5 mg) compared to women receiving placebo (35 versus 17 per 10,000 women-years). Statistically significant increases in risk for both DVT (26 versus 13 per 10,000 women-years) and PE (18 versus 8 per 10,000 women-years) were also demonstrated. The increase in VTE risk was demonstrated during the first year and persisted^3 [see Clinical Studies (14.4)]. Immediately discontinue estrogen plus progestogen therapy if a VTE occurs or is suspected.

In the WHI estrogen-alone substudy, the risk of VTE was increased for women receiving daily CE (0.625 mg)-alone compared to placebo (30 versus 22 per 10,000 women-years), although only the increased risk of DVT reached statistical significance (23 versus 15 per 10,000 women-years). The increase in VTE risk was demonstrated during the first 2 years^4 [see Clinical Studies (14.4)]. Immediately discontinue estrogen-alone therapy if a VTE occurs or is suspected.

If feasible, discontinue estrogens at least 4 to 6 weeks before surgery of the type associated with an increased risk of thromboembolism, or during periods of prolonged immobilization.

5.2 Hyperkalemia

Angeliq contains the progestin DRSP that has antialdosterone activity, including the potential for hyperkalemia in high-risk patients. Angeliq is contraindicated in patients with conditions that predispose to hyperkalemia (renal impairment, hepatic impairment, and adrenal insufficiency).

Use caution when prescribing Angeliq to women who regularly take other medications that can increase potassium, such as non-steroidal anti-inflammatory drugs (NSAIDs), potassium-sparing diuretics, potassium supplements, angiotensin converting enzyme (ACE) inhibitors, angiotensin-II receptor antagonists, heparin and aldosterone antagonists. Consider monitoring serum potassium concentrations during the first month of dosing in high-risk patients who take strong CYP3A4 inhibitors long-term and concomitantly. Strong CYP3A4 inhibitors include azole antifungals (for example, ketoconazole, itraconazole, voriconazole), human immunodeficiency virus (HIV)/hepatitis C virus (HCV) protease inhibitors (for example, indinavir, boceprevir), and clarithromycin [see Drug Interactions (7.1) and Clinical Pharmacology (12.3)].

5.3 Malignant Neoplasms

Breast Cancer

After a mean follow-up of 5.6 years, the WHI substudy of daily CE (0.625 mg) plus MPA (2.5 mg) reported an increased risk of invasive breast cancer in women who took daily CE plus MPA compared to placebo. In this substudy, prior use of estrogen-alone or estrogen plus progestin therapy was reported by 26 percent of the women. The relative risk of invasive breast cancer was 1.24 and the absolute risk was 41 versus 33 cases per 10,000 women-years, for CE plus MPA compared with placebo. Among women who reported prior use of hormone therapy, the relative risk of invasive breast cancer was 1.86 and the absolute risk was 46 versus 25 cases per 10,000 women-years for CE plus MPA compared with placebo. Among women who reported no prior use of hormone therapy, the relative risk of invasive breast cancer was 1.09 and the absolute risk was 40 versus 36 cases per 10,000 women-years for CE plus MPA compared with placebo. In the same substudy, invasive breast cancers were larger, were more likely to be node positive, and were diagnosed at a more advanced stage in the CE (0.625 mg) plus MPA (2.5 mg) group compared with the placebo group. Metastatic disease was rare, with no apparent difference between the two groups. Other prognostic factors, such as histologic subtype, grade and hormone receptor status did not differ between the groups^5 [see Clinical Studies (14.4)]

The WHI substudy of daily CE (0.625 mg)-alone provided information about breast cancer in estrogen-alone users. In the WHI estrogen-alone substudy, after an average follow-up of 7.1 years, daily CE (0.625 mg)-alone was not associated with an increased risk of invasive breast cancer [relative risk (RR) 0.80]^6 compared to placebo [see Clinical Studies (14.4)].

Consistent with the WHI clinical trial, observational studies have also reported an increased risk of breast cancer with estrogen plus progestin therapy, and a smaller increase in the risk for breast cancer with estrogen-alone therapy, after several years of use. One large meta-analysis of prospective cohort studies reported increased risks that were dependent upon duration of use and could last up to >10 years after discontinuation of estrogen plus progestin therapy and estrogen-alonetherapy. Extension of the WHI trials also demonstrated increased breast cancer risk associated with estrogen plus progestin therapy. Observational studies also suggest that the risk of breast cancer was greater, and became apparent earlier, with estrogen plus progestin therapy as compared to estrogen-alone therapy. These studies have not generally found significant variation in the risk of breast cancer among different estrogen plus progestin combinations, doses, or routes of administration.

The use of estrogen-alone and estrogen plus progestin has been reported to result in an increase in abnormal mammograms requiring further evaluation.

All women should receive yearly breast examinations by a healthcare provider and perform monthly breast self-examinations. In addition, mammography examinations should be scheduled based on patient age, risk factors, and prior mammogram results.

Endometrial Cancer

An increased risk of endometrial cancer has been reported with the use of unopposed estrogen therapy in a woman with a uterus. The reported endometrial cancer risk among unopposed estrogen users is about 2- to 12-fold greater than in non-users, and appears dependent on duration of treatment and on estrogen dose. Most studies show no significant increased risk associated with use of estrogens for less than 1 year. The greatest risk appears associated with prolonged use, with increased risks of 15- to 24-fold for 5 to 10 years or more. This risk has been shown to persist for at least 8 to 15 years after estrogen therapy is discontinued.

Clinical surveillance of all women using estrogen-alone or estrogen plus progestin therapy is important. Perform adequate diagnostic measures, including directed or random endometrial sampling when indicated, to rule out malignancy in postmenopausal women with undiagnosed persistent or recurring abnormal genital bleeding with unknown etiology.

There is no evidence that the use of natural estrogens results in a different endometrial risk profile than synthetic estrogens of equivalent estrogen dose. Adding a progestogen to estrogen therapy in postmenopausal women has been shown to reduce the risk of endometrial hyperplasia, which may be a precursor to endometrial cancer.

Ovarian Cancer

The CE plus MPA substudy of WHI reported that estrogen plus progestin increased the risk of ovarian cancer. After an average follow-up of 5.6 years, the relative risk for ovarian cancer for CE plus MPA versus placebo was 1.58 (95 percent CI 0.77-3.24) but was not statistically significant. The absolute risk for CE plus MPA versus placebo was 4 versus 3 cases per 10,000 women-years.^7

A meta-analysis of 17 prospective and 35 retrospective epidemiology studies found that women who used hormonal therapy for menopausal symptoms had an increased risk for ovarian cancer. The primary analysis, using case-control comparisons, included 12,110 cancer cases from the 17 prospective studies. The relative risks associated with current use of hormonal therapy was 1.41 (95% confidence interval [CI] 1.32 to 1.50); there was no difference in the risk estimates by duration of the exposure (less than 5 years [median of 3 years] vs. greater than 5 years [median of 10 years] of use before the cancer diagnosis). The relative risk associated with combined current and recent use (discontinued use within 5 years before cancer diagnosis) was 1.37 (95% CI 1.27 to 1.48), and the elevated risk was significant for both estrogen-alone and estrogen plus progestin products. The exact duration of hormone therapy use associated with an increased risk of ovarian cancer, however, is unknown.

5.4 Probable Dementia

In the WHI Memory Study (WHIMS) estrogen plus progestin ancillary study, a population of 4,532 postmenopausal women 65 to 79 years of age was randomized to daily CE (0.625 mg) plus MPA (2.5 mg) or placebo. After an average follow-up of 4 years, 40 women in the CE plus MPA group and 21 women in the placebo group were diagnosed with probable dementia. The relative risk of probable dementia for CE plus MPA versus placebo was 2.05 (95 percent CI, 1.21-3.48). The absolute risk of probable dementia for CE plus MPA versus placebo was 45 versus 22 cases per 10,000 women-years^8 [see Use in Specific Populations (8.5), and Clinical Studies (14.5)].

In the WHIMS estrogen-alone ancillary study, a population of 2,947 hysterectomized women 65 to 79 years of age was randomized to daily CE (0.625 mg)-alone or placebo. After an average follow-up of 5.2 years, 28 women in the estrogen-alone group and 19 women in the placebo group were diagnosed with probable dementia. The relative risk of probable dementia for CE-alone versus placebo was 1.49 (95 percent CI, 0.83-2.66). The absolute risk of probable dementia for CE-alone versus placebo was 37 versus 25 cases per 10,000 women-years^8 [see Use in Specific Populations (8.5) and Clinical Studies (14.5)].

When data from the two populations in the WHIMS estrogen-alone and estrogen plus progestin ancillary studies were pooled as planned in the WHIMS protocol, the reported overall relative risk for probable dementia was 1.76 (95 percent CI 1.19-2.60). Since both ancillary studies were conducted in women 65 to 79 years of age, it is unknown whether these findings apply to younger postmenopausal women^8 [see Use in Specific Populations (8.5) and Clinical Studies (14.5)].

5.5 Gallbladder Disease

A 2- to 4-fold increase in the risk of gallbladder disease requiring surgery in postmenopausal women receiving estrogens has been reported.

5.6 Hypercalcemia

Estrogen administration may lead to severe hypercalcemia in women with breast cancer and bone metastases. Discontinue estrogen plus progestin, including Angeliq if hypercalcemia occurs, and take appropriate measures to reduce the serum calcium concentration.

5.7 Visual Abnormalities

Retinal vascular thrombosis has been reported in women receiving estrogens. Discontinue Angeliq pending examination if there is sudden partial or complete loss of vision, or a sudden onset of proptosis, diplopia, or migraine. Permanently discontinue estrogen plus progestin, including Angeliq, if examination reveals papilledema or retinal vascular lesions.

5.8 Elevated Blood Pressure

In a small number of case reports, substantial increases in blood pressure have been attributed to idiosyncratic reactions to estrogens. In a large, randomized, placebo-controlled clinical trial, a generalized effect of estrogen therapy on blood pressure was not seen.

5.9 Exacerbation of Hypertriglyceridemia

In women with pre-existing hypertriglyceridemia, estrogen therapy may be associated with elevations of plasma triglycerides leading to pancreatitis. Discontinuation Angeliq if pancreatitis occurs.

5.10 Hepatic Impairment and/or Past History of Cholestatic Jaundice

Estrogens may be poorly metabolized in women with hepatic impairment. Exercise caution in any woman with a history of cholestatic jaundice associated with past estrogen use or with pregnancy. In the case of recurrence of cholestatic jaundice, discontinue Angeliq.

The clearance of drospirenone was decreased in patients with moderate hepatic impairment.

5.11 Exacerbation of Hypothyroidism

Estrogen administration leads to increased thyroid-binding globulin (TBG) concentrations. Women with normal thyroid function can compensate for the increased TBG by making more thyroid hormone, thus maintaining free T4 and T3 serum concentrations in the normal range. Women dependent on thyroid hormone replacement therapy who are also receiving estrogens may require increased doses of their thyroid replacement therapy. Monitor thyroid function in these women during treatment with Angeliq to maintain their free thyroid hormone concentrations in an acceptable range.

5.12 Fluid Retention

Estrogens plus progestogens may cause some degree of fluid retention. Monitor any woman with a condition(s) that might predispose her to fluid retention, such as a cardiac or renal impairment. Discontinue estrogen plus progestogen therapy, including Angeliq, with evidence of medically concerning fluid retention.

5.13 Hypocalcemia

Estrogen-induced hypocalcemia may occur in women with hypoparathyroidism. Consider whether the benefits of estrogen therapy, including Angeliq, outweigh the risks in such women.

5.14 Hyponatremia

As an aldosterone antagonist, drospirenone may increase the possibility of hyponatremia in high-risk women.

5.15 Exacerbation of Endometriosis

A few cases of malignant transformation of residual endometrial implants have been reported in women treated post-hysterectomy with estrogen-alone therapy.

5.16 Hereditary Angioedema

Exogenous estrogens may exacerbate symptoms of angioedema in women with hereditary angioedema. Consider whether the benefits of estrogen therapy, including Angeliq, outweigh the risks in such women.

5.17 Exacerbation of Other Conditions

Estrogen therapy, including Angeliq, may cause an exacerbation of asthma, diabetes mellitus, epilepsy, migraine, porphyria, systemic lupus erythematosus otosclerosis, chorea minor and hepatic hemangiomas. Consider whether the benefits of estrogen therapy outweigh the risks in women with such conditions.

5.18 Laboratory Tests

Serum follicle stimulating hormone (FSH) and estradiol concentrations have not been shown to be useful in the management of moderate to severe vasomotor symptoms.

5.19 Interference with Laboratory Tests

- Accelerated prothrombin time, partial thromboplastin time, and platelet aggregation time; increased platelet count; increased factors II, VII antigen, VIII antigen, VIII coagulant activity, IX, X, XII, VII–X complex, II–VII–X complex, and beta-thromboglobulin; decreased concentrations of anti-factor Xa and antithrombin III, decreased antithrombin III activity; increased concentrations of fibrinogen and fibrinogen activity; increased plasminogen antigen and activity.
- Increased TBG concentrations leading to increased circulating total thyroid hormone, as measured by protein-bound iodine (PBI), T4 concentrations (by column or by radioimmunoassay) or T3 concentrations by radioimmunoassay. T3 resin uptake is decreased, reflecting the elevated TBG. Free T4 and free T3 concentrations are unaltered. Women on thyroid replacement therapy may require higher doses of thyroid hormone.
- Other binding proteins may be elevated in serum, for example, corticosteroid binding globulin (CBG), sex hormone binding globulin, leading to increased total circulating corticosteroids and sex steroids, respectively. Free hormone concentrations, such as testosterone and estradiol, may be decreased. Other plasma proteins may be increased (angiotensinogen/renin substrate, alpha-l-antitrypsin, ceruloplasmin).
- Increased plasma high-density lipoprotein (HDL) and HDL2 subfraction concentrations, reduced low-density lipoprotein (LDL) cholesterol concentration, and increased triglyceride concentrations.
- Impaired glucose tolerance.

6 ADVERSE REACTIONS

The following serious adverse reactions are discussed elsewhere in the labeling:

- Cardiovascular Disorders [see Boxed Warning, Warnings and Precautions (5.1)]
- Malignant Neoplasms [see Boxed Warning, Warnings and Precautions (5.3)]

6.1 Clinical Trials Experience

Because clinical trials are conducted under widely varying conditions, adverse reaction rates observed in the clinical trials of a drug cannot be directly compared to rates in the clinical trials of another drug and may not reflect the rates observed in practice.

From clinical trials with different dose formulations of Angeliq containing E2 dose ranging from 0.5 mg to 1.0 mg combined with DRSP dose ranging from 0.25 mg to 3 mg:

- The most common adverse reactions were gastrointestinal and abdominal pain, female genital bleeding, breast pain and headache. The frequencies of common adverse reactions, in general, were higher for the Angeliq dose formulation containing E2 1 mg compared to Angeliq containing E2 0.5 mg.
- The most common adverse reactions leading to drug discontinuation in controlled clinical trials were abdominal pain, headache, postmenopausal bleeding, breast tenderness, and weight increased.

Placebo-Controlled Trial:

In a placebo-controlled trial evaluating Angeliq 0.25 mg DRSP/0.5 mg E2, 183 postmenopausal women received at least one dose of DRSP 0.25 mg/0.5 mg E2 and 180 received placebo. Study participants were treated for 3 cycles of 28 days each for a total of 12 weeks of treatment. The median age was 53 years (range: 40-77 years) and over 50% of women had a hysterectomy, 68% were Caucasian and 24% were Black. Table 1 summarizes adverse reactions reported in at least 2% of women receiving Angeliq 0.25 mg DRS/0.5 mg E2 and at a higher incidence than subjects receiving placebo.

Table 1: Adverse Reactions that Occurred at a Frequency of ≥ 2% with Angeliq 0.25 mg DRSP/0.5 mg E2 and at a Higher Incidence than Placebo
Adverse Reaction | Angeliq (0.25 mg DRSP/0.5 mg E2) N=183 (100%) n (%) | Placebo N=180 (100%) n (%)
Gastrointestinal and abdominal pains [Gastrointestinal and abdominal pain includes: abdominal pain (overall, lower, and upper), abdominal discomfort, abdominal tenderness] | 11 (6.0) | 5 (2.8)
Headache | 11 (6.0) | 9 (5.0)
Vulvovaginal fungal infections | 10 (5.5) | 1 (0.6)
Breast pain [Breast pain includes: breast pain, breast tenderness, nipple pain] | 6 (3.3) | 1 (0.6)
Nausea | 6 (3.3) | 2 (1.1)
Diarrhea | 4 (2.2) | 1 (0.6)
Peripheral Edema | 4 (2.2) | 2 (1.1)

Pooled data of clinical trials with different dose formulations of Angeliq:

Data from 13 clinical trials in postmenopausal women treated with different dose formulations of Angeliq containing 1 mg E2 (1 mg E2 + 0.5 mg – 3.0 mg DRSP; N=2842) were pooled to provide an overall estimate of adverse reactions. Similarly, data from 2 clinical trials with Angeliq containing 0.5 mg E2 (0.5 mg E2 + DRSP 0.25 mg – 0.5 mg; N=853) were pooled for the same purpose. Table 2 shows adverse reactions reported in at least 1% of women treated with Angeliq.

Table 2: Adverse Reactions that Occurred at a Frequency of ≥ 1% in Clinical Trials
Adverse Reaction | Angeliq containing 1 mg E2 N = 2842 n (%) | Angeliq containing 0.5 mg E2 N=853 n (%)
Breast pain or discomfort | 508 (17.9) | 53 (6.2)
Female genital tract bleeding | 397 (14.0) | 21 (2.5)
Gastrointestinal and abdominal pain | 186 (6.5) | 31 (3.6)
Cervical polyp | 34 (1.2) | 3 (0.4)
Emotional lability | 35 (1.2) | 11 (1.3)
Migraine | 28 (1.0) | 5 (0.6)

Adverse Reactions in clinical studies were coded using the MedDRA dictionary (version 13.0). Different MedDRA terms representing the same medical phenomenon have been grouped together as single adverse reactions to avoid diluting or obscuring the true effect.

6.2 Postmarketing Experience

The following additional adverse reactions have been reported during post-approval use of Angeliq. Because these reactions are reported voluntarily from a population of uncertain size, it is not always possible to reliably estimate their frequency or establishing a causal relationship to drug exposure.

Immune System Disorders: Hypersensitivity reactions, including rash, pruritis, and urticaria

Reproductive system and breast disorders: Breast cancer

Vascular disorders: venous and arterial thromboembolic events (peripheral deep venous occlusion, thrombosis and embolism/pulmonary vascular occlusion, thrombosis, embolism and infarction/myocardial infarction/cerebral infarction and stroke not specified as hemorrhagic)

7 DRUG INTERACTIONS

7.1 Metabolic Interactions

Effect of Drospirenone on Other Drugs

The potential effect of DRSP on CYP2C19 activity was investigated in a clinical pharmacokinetic study using omeprazole as a marker substrate. No significant effect of DRSP on the systemic clearance of the CYP3A4 product omeprazole sulfone was found. These results demonstrated that DRSP did not inhibit CYP2C19 and CYP3A4 in vivo. Two further clinical drug-drug interaction studies using simvastatin and midazolam as marker substrates for CYP3A4, respectively, were performed and the results of these studies demonstrated that pharmacokinetics of the CYP3A4 substrates were not influenced by steady-state DRSP concentrations.

Co-administration of DRSP and drugs that may increase serum potassium: There is a potential for an increase in serum potassium in women taking DRSP with other drugs that may affect electrolytes, such as ACE inhibitors, angiotensin receptor blockers, or NSAIDs, more pronounced in diabetic women [see Warnings and Precautions (5.2), and Clinical Pharmacology (12.3)].

Electrolytes were studied in postmenopausal women with hypertension and/or diabetes mellitus requiring an ACE inhibitor or angiotensin receptor blocker. After 28 days of exposure to 1 mg E2 and 3 mg DRSP (n=112) or placebo (n=118). The mean change from baseline in serum potassium was 0.11 mEq/L for the E2/DRSP group and 0.08 mEq/L for the placebo group. None of the subjects with serum potassium concentrations ≥5.5 mEq/L had cardiovascular adverse events.

A drug-drug interaction study of DRSP 3 mg/E2 1 mg versus placebo was performed in mildly hypertensive postmenopausal women taking enalapril maleate 10 mg twice daily. Potassium concentrations were obtained every other day for a total of 2 weeks in all subjects. Mean serum potassium concentrations in the DRSP/E2 treatment group relative to baseline were 0.22 mEq/L higher than those in the placebo group. On Day 14, the ratios for serum potassium Cmax and AUC in the DRSP/E2 group to those in the placebo group were 0.955 (90% CI: 0.914, 0.999) and 1.01 (90% CI: 0.944, 1.08), respectively. No woman in either treatment group developed hyperkalemia (serum potassium concentrations >5.5 mEq/L).

Of note, occasional or chronic use of NSAID medication was not restricted in any of the Angeliq clinical trials.

Effect of Other Drugs on Estrogens and Progestins

In vitro and in vivo studies have shown that estrogens and progestins are metabolized partially by cytochrome P450 3A4 (CYP3A4). Therefore, inducers or inhibitors of CYP3A4 may affect estrogen drug metabolism. In a clinical drug-drug interaction study conducted in premenopausal women, once daily co-administration of DRSP 3 mg/E2 1.5 mg containing tablets with strong CYP3A4 inhibitor, ketoconazole 200 mg twice daily for 10 days resulted in a moderate increase of exposure and a mild increase of peak concentration for DRSP. The E2 exposure and peak concentration were unaffected by ketoconazole, although the exposure and peak concentration of estrone (E1) increased. Although no clinically relevant effects on any safety or laboratory parameters including serum potassium were observed, this study only assessed women for 10 days. The clinical impact for a woman taking a DRSP-containing combination hormone and chronic use of a CYP3A4/5 inhibitor is unknown.

Substances decreasing the exposure and possibly diminishing the efficacy of estrogens and progestins (enzyme inducers)

Inducers of CYP3A4 such as St. John's wort (Hypericum perforatum), phenobarbital, carbamazepine, and rifampin may reduce plasma concentrations of estrogens and progestins, possibly resulting in a decrease in therapeutic effects and/or changes in the uterine bleeding profile.

Substances increasing the exposure of estrogens and progestins (enzyme inhibitors)

Concomitant administration of moderate or strong CYP3A4 inhibitors such as azole antifungals (for example, ketoconazole, itraconazole, voriconazole, fluconazole), verapamil, macrolides (for example, clarithromycin, erythromycin), diltiazem, and grapefruit juice did increase the plasma concentrations of the estrogen or the progestin or both [see Warnings and Precautions (5.2) and Clinical Pharmacology (12.3)].

HIV/HCV protease inhibitors and non-nucleoside reverse transcriptase inhibitors

Significant changes (increase or decrease) in the plasma concentrations of estrogen and progestin have been noted in some cases of co-administration with HIV/HCV protease inhibitors or with non-nucleoside reverse transcriptase inhibitors.

7.2 Interaction with Alcohol

Acute alcohol ingestion during use of hormone therapy may lead to elevations of circulating E2 concentrations.

8 USE IN SPECIFIC POPULATIONS

8.1 Pregnancy

Risk Summary

Angeliq is not indicated for use in pregnancy. There are no data with the use of Angeliq in pregnant women, however, epidemiologic studies and meta-analyses have not found an increased risk of genital or nongenital birth defects (including cardiac anomalies or limb-reduction defects) following exposure to combined hormonal contraceptives (estrogens and progestins) before conception or during early pregnancy.

In reproduction studies in rats, rabbits and monkeys with oral administration of DRSP either as single compound or in combination with EE, no non-genital teratogenicity was observed. Adverse developmental outcomes like an increase in fetal mortality and a retardation of fetal maturation were seen in rats and rabbits at exposures to DRSP exceeding the human exposure by a factor of >15 (in rats) or >60 (rabbits). Related to the antiandrogenic activity of drospirenone, a feminization of male fetuses and an impairment of male fertility was observed in rats (>150 times the human exposure to drospirenone) but not in monkeys (at up to more than 300 times the human exposure to drospirenone). Due to the large safety margins observed in the animal studies only a low likelihood of an increased risk for human pregnancy was concluded (see Data).

In the U.S. general population, the estimated background risk of major birth defects and miscarriage in clinically recognized pregnancies is 2% to 4% and 15% to 20%, respectively.

Data

Animal Data

In an embryo-fetal toxicity study in pregnant rats, DRSP was given from day 6 to 15 of gestation orally at doses of 5, 15 and 45 mg/kg/day, more than 60 times the human exposure starting from the low dose based on AUC of DRSP. A slight increase in postimplantational loss and a slight increase in retardation of fetal development (e.g. delayed ossification of bones of the feet) was seen in the two higher doses. No teratogenicity was observed in rats.

In an embryo-fetal study in rabbits, DRSP was given from day 6 to 18 of gestation orally at doses of 10, 30 and 100 mg/kg/day, about 20, 60 and 250 times the human exposure based on AUC. This resulted in a retardation of fetal development (delayed ossification of small bones, multiple fusions of ribs) at the high dose only and in an increase in fetal loss from the mid dose level. No compound-related teratogenicity was seen in rabbits.

In a further embryo-fetal toxicity study in pregnant rats, DRSP was orally administered in combination with ethinyl estradiol (100:1) from day 6 to 17 of gestation at doses of 1, 3 and 10 mg/kg/day DRSP, at about 1, 3 and 23 times the human exposure to DRSP on basis of AUC. Maternal toxicity (decreased body weight gain and food consumption) was seen starting at the low dose and an increase of early resorptions at the high dose level. Skeletal variations and retardations were seen in fetuses at the high dose. No malformed fetuses and no effect on the external genitalia of the fetuses were observed.

DRSP was administered with ethinyl estradiol (100:1) orally to pregnant rats during late pregnancy from day 14 to 21 of gestation (the period of genital development) at doses of 5, 15 and 45 mg/kg of DRSP, more than 60 times the human exposure starting from the low dose based on AUC of DRSP. Maternal toxicity (decreased body weight gain) and fetal retardation (decreased fetal body weights) were seen starting at the low dose. There was a dose dependent increase in feminization of male rat fetuses starting at the mid dose level (that is, >150 times the human exposure to DRSP).

DRSP was administered with ethinyl estradiol (100:1) orally to pregnant cynomolgus monkeys at doses up to 10 mg/kg DRSP, more than 300 times the human exposure based on AUC from day 20 to 90 of gestation. A dose-dependent increase of abortions was observed. No teratogenic or feminization effects were seen in any dose group.

DRSP was administered with ethinyl estradiol (100:1) in a peri-postnatal study in rats from day 6 to 16 of gestation and day 1 to 22 postpartum at doses of 5, 15 and 45 mg/kg; more than 60 times the human exposure starting from the low dose based on AUC of DRSP. There was a dose dependent delay in fetal development and an increase in mortality of the F1-generation during the lactational phase. Fertility was impaired in the male offspring at the high dose level.

8.2 Lactation

Risk Summary

Estrogens plus progestogens are present in human milk and can reduce milk production in breast-feeding women. This reduction can occur at any time but is less likely to occur once breast-feeding is well established. After administration of an oral contraceptive containing DRSP about 0.02% of the DRSP dose was excreted into the breast milk of postpartum women within 24 hours. This results in a maximal daily dose of about 3 mcg DRSP in an infant. The developmental and health benefits of breastfeeding should be considered along with the mother's clinical need for Angeliq and any potential adverse effects on the breastfed infant from Angeliq or from the underlying maternal condition.

8.4 Pediatric Use

Angeliq is not indicated for use in pediatric patients. Clinical studies have not been conducted in the pediatric population.

8.5 Geriatric Use

There have not been sufficient numbers of geriatric women involved in clinical studies utilizing Angeliq to determine whether those over 65 years of age differ from younger women in their response to Angeliq.

The Women's Health Initiative Studies

In the WHI estrogen plus progestin substudy (daily CE [0.625 mg] plus MPA [2.5 mg] versus placebo), there was a higher relative risk of nonfatal stroke and invasive breast cancer in women greater than 65 years of age [see Warnings and Precautions (5.1, 5.3) and Clinical Studies (14.4)].

In the WHI estrogen-alone substudy (daily CE [0.625 mg] versus placebo), there was a higher relative risk of stroke in women greater than 65 years of age [see Warnings and Precautions (5.1) and Clinical Studies (14.4)].

The Women's Health Initiative Memory Study

In the WHIMS ancillary studies of postmenopausal women 65 to 79 years of age, there was an increased risk of developing probable dementia in women receiving estrogen plus progestin or estrogen-alone when compared to placebo [see Warnings and Precautions (5.4), and Clinical Studies (14.5)].

Since both ancillary studies were conducted in women 65 to 79 years of age, it is unknown whether these findings apply to younger postmenopausal women^8 [see Warnings and Precautions (5.4), and Clinical Studies (14.5)].

8.6 Renal Impairment

Angeliq is contraindicated in patients with renal impairment because of the risk of hyperkalemia [see Contraindications (4), Warnings and Precautions (5.2) and Clinical Pharmacology (12.3)].

8.7 Hepatic Impairment

Angeliq is contraindicated in patients with hepatic impairment because of the risk of increased DRSP exposure and subsequent hyperkalemia [see Contraindications (4), Warnings and Precautions (5.10) and Clinical Pharmacology (12.3)].

8.8 Adrenal Insufficiency

Angeliq is contraindicated in patients with adrenal insufficiency because of the risk of hyperkalemia [see Contraindications (4) and Warnings and Precautions (5.2)].

10 OVERDOSAGE

Overdosage of estrogen plus progestogen may cause nausea and vomiting, breast tenderness, abdominal pain, drowsiness and fatigue, and withdrawal bleeding may occur in women. Treatment of overdose consists of discontinuation of Angeliq therapy with institution of appropriate symptomatic care.

11 DESCRIPTION

Angeliq tablets, for oral administration, provide a hormone regimen consisting of drospirenone and estradiol.

Drospirenone, (6R,7R,8R,9S,10R,13S,14S,15S,16S,17S)-1,3´,4´,6, 6a,7,8,9,10,11,12,13,14,15,15a,16-hexadecahydro-10,13-dimethylspiro-[17H-dicyclopropa[6,7:15,16]cyclopenta[a]phenanthrene- 17,2´(5H)-furan]-3,5´(2H)-dione (CAS) is a synthetic progestational compound and has a molecular weight of 366.5 and a molecular formula of C24H30O3.

Estradiol USP, (Estra-1,3,5(10)-triene-3,17-diol,17ß), has a molecular weight of 272.39 and the molecular formula is C18H24O2. The structural formulas are as follows:

The inactive ingredients in Angeliq 0.5 mg DRSP/1 mg E2 tablets are: lactose monohydrate NF, corn starch NF, pregelatinized starch NF, povidone 25000 USP, magnesium stearate NF, hydroxylpropylmethyl cellulose USP, macrogol 6000 NF, talc USP, titanium dioxide USP, and red ferric oxide pigment NF.

The inactive ingredients in Angeliq 0.25 mg DRSP/0.5 mg E2 tablets are: lactose monohydrate NF, corn starch NF, pregelatinized starch NF, povidone 25000 USP, magnesium stearate NF, hydroxylpropylmethyl cellulose USP, macrogol 6000 NF, talc USP, titanium dioxide USP, and yellow ferric oxide pigment NF.

12 CLINICAL PHARMACOLOGY

12.1 Mechanism of Action

Endogenous estrogens are largely responsible for the development and maintenance of the female reproductive system and secondary sexual characteristics. Although circulating estrogens exist in a dynamic equilibrium of metabolic interconversions, estradiol (E2) is the principal intracellular human estrogen and is substantially more potent than its metabolites, estrone and estriol, at the receptor level.

The primary source of estrogen in normally cycling adult women is the ovarian follicle, which secretes 70 to 500 mcg of estradiol daily, depending on the phase of the menstrual cycle. After menopause, most endogenous estrogen is produced by conversion of androstenedione, secreted by the adrenal cortex, to estrone in the peripheral tissues. Thus, estrone and the sulfate-conjugated form, estrone sulfate, are the most abundant circulating estrogens in postmenopausal women.

Estrogens act through binding to nuclear receptors in estrogen-responsive tissues. To date, two estrogen receptors have been identified. These will vary in proportion from tissue to tissue.

Circulating estrogens modulate the pituitary secretion of the gonadotropins, luteinizing hormone (LH), and follicle-stimulating hormone (FSH), through a negative feedback mechanism. Estrogens act to reduce the elevated concentrations of these gonadotropins seen in postmenopausal women.

DRSP is a synthetic progestin and spironolactone analog with antimineralocorticoid activity. In animals and in vitro, drospirenone has antiandrogenic activity, but no glucocorticoid, antiglucocorticoid, estrogenic, or androgenic activity. Progestins counter estrogenic effects by decreasing the number of nuclear estradiol receptors and suppressing epithelial DNA synthesis in endometrial tissue.

12.2 Pharmacodynamics

Generally, a serum estrogen concentration does not predict an individual woman's therapeutic response to Angeliq nor her risk for adverse outcomes. Likewise, exposure comparisons across different estrogen plus progestin products to infer efficacy or safety for the individual woman may not be valid.

12.3 Pharmacokinetics

Absorption

Serum concentrations of DRSP reach peak concentrations approximately 1 hour after administration of Angeliq and mean absolute bioavailability of DRSP ranges from 76–85%. Following oral administration, the median Tmax of serum estradiol was approximately 2 hours after dosing with Angeliq and Tmax ranged between 0.3-10 hours.

The pharmacokinetics of DRSP are dose proportional within the dose range of 0.25–4 mg. Following daily dosing of Angeliq, steady state DRSP concentrations were observed after 10 days. Mean accumulation ratios for DRSP and estradiol were 2.3 and 2.0, respectively, following multiple doses of 0.5 mg DRSP/1 mg E2, and 2.6 and 1.6, respectively, following multiple doses of 0.25 mg DRSP/0.5 mg E2. Mean concentrations at 2 hours for DRSP ranged between 5.9 and 6.7 ng/mL after treatment with Angeliq (0.5 mg DRSP/1 mg E2) for 365 days. Mean steady state serum DRSP and E2 concentrations are shown in Figure 1, and a summary of primary pharmacokinetic parameters following the administration of 0.25 mg DRSP/0.5 mg E2 or 0.5 mg DRSP/1 mg E2 at steady state is presented in Table 3.

Figure 1: Mean (± SD) steady state serum drospirenone and estradiol concentrations following daily oral administration of 0.25 or 0.5 mg Drospirenone and 0.5 or 1 mg Estradiol

0.25 mg DRSP/0.5 mg E2

0.5 mg DRSP/1 mg E2

Table 3: Mean (± SD) Steady State Pharmacokinetic Parameters after Administration of Tablets Containing 0.25 or 0.5 mg Drospirenone and 0.5 or 1 mg Estradiol
Parameter | Unit | 0.25 mg DRSP/0.5 mg E2 | 0.5 mg DRSP/1 mg E2
Drospirenone (DRSP) |  | N=12 | N=17
Cmax | ng/mL | 5.70 (1.42) | 8.50 (1.63)
Tmax | h | 0.992 (0.667 – 1.03) | 1.02 (1 – 2.03)
AUC (0-24) | ng∙h/mL | 48.5 (13.7) | 84.3 (19.7)
t1/2 | h | N/A | 39.2 [N=16] (8.5)
Estradiol (E2)
Cmax | pg/mL | 29.7 (6.80) | 63.7 (24.2)
Tmax | h | 2.33 (0.32 – 10) | 2.01 (0.5 – 6.02)
AUC (0-24) | pg∙h/mL | 515.4 (142.0) | 882 (267)
t1/2 | h | N/A | 20.5 (2.67)
Estrone (E1)
Cmax | pg/mL | 165.7 (40.4) | 362 (122)
Tmax | h | 3.98 (1.98 – 7.05) | 6 (3.99 – 10)
AUC (0-24) | pg∙h/mL | 2839 (658) | 5561 (1689)
t1/2 | h | N/A | 19.9 (2.10)
Except for Tmax, the mean PK results of DRSP, E2, and E1 are displayed as the arithmetic mean and standard deviation (SD, in parentheses). For Tmax the median and range are provided.
Cmax=Maximum observed serum concentration
Tmax=time to reach Cmax
AUC (0-24)=area under the serum concentration-time curve from 0 h up to 24 h after daily multiple administration
t1/2=half-life
N/A=Not available

Effect of Food

The effect of food on the absorption and bioavailability of DRSP and E2 have not been investigated following the administration of Angeliq. However, clinical studies with different formulations containing DRSP or E2 have shown that the bioavailability of both drugs is not affected by concomitant food intake.

Distribution

The mean volume of distribution of DRSP is 4.2 L/kg. DRSP does not bind to SHBG or CBG but binds about 97% to other serum proteins. The distribution of exogenous estrogens is similar to that of endogenous estrogens. Estrogens are widely distributed in the body and are generally found in higher concentrations in the sex hormone target organs. Estradiol circulates in the blood bound to SHBG (37%) and to albumin (61%), while only approximately 1%–2% is unbound.

Metabolism

Mean clearance of DRSP is 1.2 mL/min/kg. DRSP is extensively metabolized after oral administration. The two main metabolites of DRSP found in human plasma were identified to be the acid form of DRSP generated by opening of the lactone ring and the 4,5-dihydrodrospirenone-3-sulfate, formed by reduction and subsequent sulfation. These metabolites were shown not to be pharmacologically active. DRSP is also subject to oxidative metabolism catalyzed by CYP 3A4.

Exogenous estrogens are metabolized in the same manner as endogenous estrogens. Circulating estrogens exist in a dynamic equilibrium of metabolic interconversions. These transformations take place mainly in the liver. Estradiol is converted reversibly to estrone, and both can be converted to estriol, which is a major urinary metabolite. Estrogens also undergo enterohepatic recirculation via sulfate and glucuronide conjugation in the liver, biliary secretion of conjugates into the intestine, and hydrolysis in the gut followed by reabsorption. In postmenopausal women, a significant proportion of the circulating estrogens exist as sulfate conjugates, especially estrone sulfate, which serves as a circulating reservoir for the formation of more active estrogens.

Excretion

DRSP serum concentrations are characterized by a terminal elimination half-life of approximately 36–42 hours. Excretion of DRSP was nearly complete after 10 days and amounts excreted were slightly higher in feces compared to urine. DRSP was extensively metabolized and only trace amounts of unchanged DRSP were excreted in urine and feces. At least 20 different metabolites were observed in urine and feces. About 38% to 47% of the metabolites in urine were glucuronide and sulfate conjugates. In feces, about 17% to 20% of the metabolites were excreted as glucuronides and sulfates. Estradiol, estrone, and estriol are excreted in the urine along with glucuronide and sulfate conjugates.

Hepatic Impairment

Angeliq is contraindicated in patients with hepatic impairment [see Contraindications (4) and Warnings and Precautions (5.10)]. The mean exposure to DRSP in women with moderate liver impairment is approximately three times the exposure in women with normal liver function.

Renal Impairment

Angeliq is contraindicated in patients with renal impairment [see Contraindications (4) and Warnings and Precautions (5.2)].

The effect of renal impairment on the pharmacokinetics of DRSP (3 mg daily for 14 days) and the effects of DRSP on serum potassium concentrations were investigated in female subjects (n=28, age 30-65 years) with creatinine clearance (CLcr) ≥ 80 mL/min (11 patients), and CLcr of 50-79 mL/min (10 patients) and CLcr of 30-49 mL/min (7 patients). All subjects were on a low potassium diet. During the study 7 subjects continued the use of potassium-sparing drugs for the treatment of the underlying illness. On the 14th day (steady-state) of DRSP treatment, the serum DRSP concentrations were on average 37% higher in the group with CLcr of 30-49 mL/min compared to those in the group with normal renal function (CLcr ≥ 80 mL/min). Serum DRSP concentrations in the group with CLcr of 50–79 mL/min were comparable to those in the group with CLcr ≥ 80 mL/min. DRSP treatment was well tolerated by all groups. DRSP treatment did not show any clinically significant effect on serum potassium concentration. Although hyperkalemia was not observed in the study, in 5 of the 7 subjects who continued use of potassium sparing drugs during the study, individual mean serum potassium concentrations increased by up to 0.33 mEq/L. Therefore, potential exists for hyperkalemia to occur in subjects with renal impairment whose serum potassium is in the upper reference range, and who are concomitantly using potassium sparing drugs.

Effects of Drospirenone on Other Drugs: Metabolism of DRSP and potential effects of DRSP on hepatic CYP enzymes have been investigated in in vitro and in vivo studies. In in vitro studies, DRSP did not affect turnover of model substrates of CYP1A2 and CYP2D6, but had an inhibitory influence on the turnover of model substrates of CYP1A1, CYP2C9, CYP2C19 and CYP3A4 with CYP2C19 being the most sensitive enzyme.

The potential effect of DRSP on CYP2C19 activity was investigated in a clinical pharmacokinetic study using omeprazole as a marker substrate. In the study with 24 postmenopausal women [including 12 women with homozygous (wild type) CYP2C19 genotype and 12 women with heterozygous CYP2C19 genotype] the daily oral administration of 3 mg DRSP for 14 days did not affect the systemic clearance of the CYP2C19 substrate omeprazole (40 mg) and the CYP2C19 product 5-hydroxy-omeprazole. Furthermore, no significant effect of DRSP on the systemic clearance of the CYP3A4 product omeprazole sulfone was found. These results demonstrated that DRSP did not inhibit CYP2C19 and CYP3A4 in vivo.

Two further clinical drug-drug interaction studies using simvastatin and midazolam as marker substrates for CYP3A4 were each performed in 24 healthy, postmenopausal women. The results of these studies demonstrated that pharmacokinetics of the CYP3A4 substrates were not influenced by steady-state DRSP concentrations achieved after administration of 3 mg DRSP/day.

Based on the available results of in vivo and in vitro studies, it can be concluded that, at clinical dose concentration, DRSP is unlikely to inhibit significantly CYP enzymes.

There is a potential for an increase in serum potassium in women taking drospirenone with other drugs that may affect electrolytes, such as ACE inhibitors, angiotensin receptor blockers, or NSAIDs.

Electrolytes were studied in 230 postmenopausal women with hypertension and/or diabetes mellitus requiring an ACE inhibitor or angiotensin receptor blocker. Of these, 26 patients had a creatinine clearance >50 mL/min to <80 mL/min. Participants were given 1 mg E2 and 3 mg DRSP (n=112) or placebo (n=118) over 28 days. Non-diabetic women also received ibuprofen 1200 mg/day for 5 days during the study. There was a single case of serum potassium >6 mEq/L and a single case of serum sodium <130 mEq/L on treatment, both occurring following five days of ibuprofen therapy in two women taking E2/DRSP. Serum potassium concentrations ≥5.5 mEq/L were observed in 8 (7.3%) E2/DRSP-treated women (3 diabetic and 5 non-diabetic) and in 3 (2.6%) placebo-treated subjects (2 diabetic and 1 non-diabetic). After 28 days of exposure, the mean change from baseline in serum potassium was 0.11 mEq/L for the E2/DRSP group and 0.08 mEq/L for the placebo group. None of the women with serum potassium concentrations ≥5.5 mEq/L had cardiovascular adverse events.

A drug-drug interaction study of DRSP 3 mg/E2 1 mg versus placebo was performed in 24 mildly hypertensive postmenopausal women taking enalapril maleate 10 mg twice daily. Potassium concentrations were obtained every other day for a total of 2 weeks in all women. Mean serum potassium concentrations in the DRSP/E2 treatment group relative to baseline were 0.22 mEq/L higher than those in the placebo group. Serum potassium concentrations also were measured at multiple timepoints over 24 hours at baseline and on Day 14. On Day 14, the ratios for serum potassium Cmax and AUC in the DRSP/E2 group to those in the placebo group were 0.955 (90% CI: 0.914, 0.999) and 1.01 (90% CI: 0.944, 1.08), respectively. No woman in either treatment group developed hyperkalemia (serum potassium concentrations >5.5 mEq/L).

Of note, occasional or chronic use of NSAID medication was not restricted in any of the Angeliq clinical trials.

Effects of Other Drugs on Estrogens and Progestins: In vitro and in vivo studies have shown that estrogens and progestins are metabolized partially by CYP3A4. Therefore, inducers or inhibitors of CYP3A4 may affect estrogen and progestin drug metabolism [see Drug Interactions (7.1)]. In a clinical drug-drug interaction study conducted in 18 premenopausal women, once daily co-administration of DRSP 3 mg/E2 1.5 mg combination tablets with strong CYP3A4 inhibitor, ketoconazole 200 mg twice daily for 10 days resulted in a 2.30-fold (90% CI: 2.08-2.54) increase of the AUC (0-24) and a 1.66-fold (90% CI: 1.50-1.84) increase of Cmax for DRSP. The E2 exposure [that is, AUC (0-24) and Cmax] was unaffected by ketoconazole, although the AUC(0-24) and Cmax for E1 increased 1.39-fold (90% CI: 1.27-1.52) and 1.32-fold (90% CI: 1.23-1.42), respectively.

13 NONCLINICAL TOXICOLOGY

13.1 Carcinogenesis, Mutagenesis, Impairment of Fertility

In a 24-month oral carcinogenicity study in mice dosed with 10 mg/kg/day DRSP alone or 1+0.01, 3+0.03 and 10+0.1 mg/kg/day of DRSP and ethinyl estradiol, 0.24 to 10.3 times the exposure (AUC of drospirenone) of women taking a 1 mg dose, there was an increase in carcinomas of the Harderian gland in the group that received the high dose of drospirenone alone. In a similar study in rats given 10 mg/kg/day drospirenone alone or 0.3+0.003, 3+0.03 and 10+0.1 mg/kg/day drospirenone and ethinyl estradiol, 2.3 to 51.2 times the exposure of women taking a 1 mg dose, there was an increased incidence of benign and total (benign and malignant) adrenal gland pheochromocytomas in the group receiving the high dose of drospirenone. Drospirenone was not mutagenic in a number of in vitro (Ames, Chinese Hamster Lung gene mutation and chromosomal damage in human lymphocytes) and in vivo (mouse micronucleus) genotoxicity tests. Drospirenone increased unscheduled DNA synthesis in rat hepatocytes and formed adducts with rodent liver DNA but not with human liver DNA.

14 CLINICAL STUDIES

14.1 Effects on Vasomotor Symptoms in Postmenopausal Women

Angeliq 0.25 mg DRSP/0.5 mg E2

The efficacy of Angeliq 0.25 mg DRSP/0.5 mg E2 for reducing the frequency and severity of moderate to severe vasomotor symptoms was evaluated in a randomized, double-blind, placebo-controlled trial. A total of 735 postmenopausal women ≥ 40 years of age with a minimum of 7 to 8 moderate to severe hot flashes daily or 50 to 60 moderate to severe hot flashes weekly were randomized to one of the two doses of Angeliq, including DRSP 0.25 mg/0.5 mg E2, estrogen monotherapy, or placebo. The median age of study participants was 53 years and 68% were Caucasian. Efficacy for vasomotor symptoms was assessed during the 12 weeks of treatment. Compared to placebo, women receiving Angeliq 0.25 mg DRSP/0.5 mg E2 achieved statistically significant reduction in the frequency and severity of moderate to severe vasomotor symptoms at Week 4 and at Week 12. The mean difference in daily reduction of frequency of hot flushes between Angeliq 0.25 mg DRSP/0.5 mg E2 and placebo were approximately -2 episodes at Week 4 and -3 episodes at Week 12. Table 4 shows the mean number of hot flushes in the Angeliq 0.25 mg DRSP/0.5 mg E2 and placebo groups and the treatment difference between Angeliq 0.25 mg DRSP/0.5 mg E2 and placebo treatment at Week 4 and at Week 12.

Table 4: Summary Tabulation of the Number of Hot Flushes Per Day – Mean Values and Comparisons Between the Active Treatment Group and the Placebo Group, Last Observation Carried Forward
Treatment | No. of Hot Flushes/Day
Time Period (week) | Baseline Mean | Mean Change from Baseline [Mean change from baseline, difference from placebo, 95% confidence interval, and p-value based on an ANCOVA model with treatment and pooled center as factors and baseline measurement as covariate] | Difference from Placebo (95% CI) | p-Values vs. Placebo
DRSP/E2 (0.25 mg/0.5 mg) [n=175]
Week 4 | 10.68 | -5.46 | -2.02 (-2.89, -1.16) | <0.0001
Week 12 | 10.68 | -7.71 | -3.17 (-3.97, -2.37) | <0.0001
Placebo [n=176]
Week 4 | 10.53 | -3.44 | - | -
Week 12 | 10.53 | -4.54 | - | -

Angeliq 0.5 mg DRSP/1 mg E2

Support for treatment of vasomotor symptoms and vaginal and vulvar atrophy was shown through bioequivalence of the E2 component of the Angeliq combination product with a currently marketed 1 mg E2 product. The multiple-dose bioequivalence study evaluated the bioequivalence of E2 from a tablet containing DRSP (2 mg) and E2 (1 mg) relative to E2 1 mg tablet. Angeliq 0.5 mg DRSP/1 mg E2 tablets met the criteria for bioequivalence to the E2 1 mg comparator.

14.2 Effects on Endometrium in Postmenopausal Women

Angeliq 0.25 mg DRSP/0.5 mg E2

In a one year clinical trial, 661 postmenopausal women were treated with Angeliq 0.25 mg DRSP/0.5 mg E2 (N=489) or a comparator drug (N=172). Endometrial biopsies were performed on 407 (83.2%) women in the Angeliq group during the treatment period. No endometrial hyperplasias occurred during or after one year of treatment. See Table 5.

Angeliq 0.5 mg DRSP/1 mg E2

In a one year clinical trial of 1,142 postmenopausal women treated with 1 mg E2 alone or 1 mg E2 + 0.5, 1, 2, or 3 mg DRSP, endometrial biopsies were performed on 966 (84.6%) women during the treatment period. Eight women in the E2 monotherapy group developed endometrial hyperplasia (4 simple hyperplasia with no cytological atypia, 3 complex hyperplasia with no cytological atypia, and 1 complex hyperplasia with cytological atypia), and one woman in the 1 mg E2+2 mg DRSP group developed simple hyperplasia with no cytological atypia. Table 5 shows that there were no diagnoses of endometrial hyperplasia in the Angeliq group.

Table 5: Incidence of Endometrial Hyperplasia after up to 12 Months of Treatment
 | E2 1 mg | Angeliq 0.25 mg DRSP/0.5 mg E2 | Angeliq 0.5 mg DRSP/1 mg E2
Total No. Subjects Treated | 226 | 489 | 227
Total No. of On-Treatment Biopsies [Includes evaluable and unevaluable endometrial biopsy results] | 197 (87.2%) | 407 (83.2%) | 191 (84.1%)
Hyperplasia | 8 (4%) | 0 (0%) | 0 (0%)

14.3 Effects on Uterine Bleeding or Spotting in Postmenopausal Women

Angeliq 0.5 mg DRSP/1 mg E2 and Angeliq 0.25 mg DRSP /0.5 mg E2 were evaluated in separate one-year clinical trials investigating the endometrial safety in postmenopausal women with an intact uterus.

Over 12 months in the double-blind trials, the proportions of women with any bleeding or spotting decreased over time. At one year, approximately 22% of women treated with Angeliq 0.5 mg/E2 1.0 mg and 15% of women treated with Angeliq 0.25 mg/E2 0.5 mg had any uterine bleeding or spotting. See Figure 2.

Figure 2: Proportion of Subjects with Any Bleeding/spotting by Month of Angeliq Use

14.4 Women's Health Initiative Studies

The WHI enrolled approximately 27,000 predominantly healthy postmenopausal women in two substudies to assess the risks and benefits of daily oral CE (0.625 mg)-alone or in combination with MPA (2.5 mg) compared to placebo in the prevention of certain chronic diseases. The primary endpoint was the incidence of CHD defined as nonfatal MI, silent MI and CHD death], with invasive breast cancer as the primary adverse outcome. A "global index" included the earliest occurrence of CHD, invasive breast cancer, stroke, PE, endometrial cancer (only in the CE plus MPA substudy), colorectal cancer, hip fracture, or death due to other cause. These substudies did not evaluate the effects of CE plus MPA or CE-alone on menopausal symptoms.

WHI Estrogen plus Progestin Substudy

The WHI estrogen plus progestin substudy was stopped early. According to the predefined stopping rule, after an average follow-up of 5.6 years of treatment, the increased risk of breast cancer and cardiovascular events exceeded the specified benefits included in the "global index." The absolute excess risk of events included in the "global index" was 19 per 10,000 women-years.

For those outcomes included in the WHI "global index" that reached statistical significance after 5.6 years of follow-up, the absolute excess risks per 10,000 women-years in the group treated with CE plus MPA were 7 more CHD events, 8 more strokes, 10 more PEs, and 8 more invasive breast cancers, while the absolute risk reductions per 10,000 women-years were 6 fewer colorectal cancers and 5 fewer hip fractures.

Results of the CE plus MPA substudy, which included 16,608 women (average 63 years of age, range 50 to 79; 83.9 percent White, 6.8 percent Black, 5.4 percent Hispanic, 3.9 percent Other) are presented in Table 6. These results reflect centrally adjudicated data after an average follow-up of 5.6 years.

Table 6: Relative and Absolute Risk Seen in the Estrogen Plus Progestin Substudy of WHI at an Average of 5.6 Years [Adapted from numerous WHI publications. WHI publications can be viewed at www.nhlbi.nih.gov/whi.] , [Results are based on centrally adjudicated data.]
Event | Relative Risk CE/MPA vs. Placebo (95% nCI [Nominal confidence intervals unadjusted for multiple looks and multiple comparisons.]) | CE/MPA n=8,506 | Placebo n=8,102
Event | Relative Risk CE/MPA vs. Placebo (95% nCI [Nominal confidence intervals unadjusted for multiple looks and multiple comparisons.]) | Absolute Risk per 10,000 Women-Years
CHD events | 1.23 (0.99–1.53) | 41 | 34
Non-fatal MI | 1.28 (1.02–1.632) | 31 | 25
CHD death | 1.10 (0.70–1.75) | 8 | 8
All strokes | 1.31 (1.03–1.68) | 33 | 25
Ischemic stroke | 1.44 (1.09-1.90) | 26 | 18
Deep vein thrombosis [Not included in "global index."] | 1.95 (1.43-2.67) | 26 | 13
Pulmonary embolism | 2.13 (1.45–3.11) | 18 | 8
Invasive breast cancer [Includes metastatic and non-metastatic breast cancer, with the exception of in situ breast cancer.] | 1.24 (1.01-1.54) | 41 | 33
Colorectal cancer | 0.61 (0.42–0.87) | 10 | 16
Endometrial cancer | 0.81 (0.48–1.36) | 6 | 7
Cervical cancer | 1.44 (0.47-4.42) | 2 | 1
Hip fracture | 0.67 (0.47–0.96) | 11 | 16
Vertebral fractures | 0.65 (0.46–0.92) | 11 | 17
Lower arm/wrist fractures | 0.71 (0.59-0.85) | 44 | 62
Total fractures | 0.76 (0.69-0.83) | 152 | 199
Overall Mortality [All deaths, except from breast or colorectal cancer, definite or probable CHD, PE or cerebrovascular disease.] | 1.00 (0.83-1.19) | 52 | 52
Global Index [A subset of the events was combined in a "global index", defined as the earliest occurrence of CHD events, invasive breast cancer, stroke, pulmonary embolism, colorectal cancer, hip fracture, or death due to other causes.] | 1.13 (1.02-1.25) | 184 | 165

Timing of the initiation of estrogen therapy relative to the start of menopause may affect the overall risk benefit profile. The WHI estrogen plus progestin substudy stratified by age showed in women 50-59 years of age, a non-significant trend toward reduced risk for overall mortality [HR 0.69 (95 percent CT 0.44-1.07)].

WHI Estrogen-Alone Substudy

The WHI estrogen-alone substudy was stopped early because an increased risk of stroke was observed, and it was deemed that no further information would be obtained regarding the risks and benefits of estrogen alone in predetermined primary endpoints.

Results of the estrogen-alone substudy, which included 10,739 women (average age of 63 years, range 50 to 79; 75.3 percent White, 15.1 percent Black, 6.1 percent Hispanic, 3.6 percent Other), after an average follow-up of 7.1 years are presented in Table 7.

Table 7. Relative and Absolute Risk Seen in the Estrogen-Alone Substudy of WHI [Adapted from numerous WHI publications. WHI publications can be viewed at www.nhlbi.nih.gov/whi.]
Event | Relative Risk CE vs. Placebo | CE n=5,310 | Placebo n=5,429
Event | (95% nCI [Nominal confidence intervals unadjusted for multiple looks and multiple comparisons,]) | Absolute Risk per 10,000 Women-Years
CHD events [Results are based on centrally adjudicated data for an average follow-up of 7.1 years.] | 0.95 (0.78–1.16) | 54 | 57
Non-fatal MI | 0.91 (0.73–1.14) | 40 | 43
CHD death | 1.01 (0.71–1.43) | 16 | 16
All stroke | 1.33 (1.05–1.68) | 45 | 33
Ischemic | 1.55 (1.19-2.01) | 38 | 25
Deep vein thrombosis, [Not included in "global index."] | 1.47 (1.06-2.06) | 23 | 15
Pulmonary embolism | 1.37 (0.90–2.07) | 14 | 10
Invasive breast cancer | 0.80 (0.62-1.04) | 28 | 34
Colorectal cancer | 1.08 (0.75–1.55) | 17 | 16
Hip fracture | 0.65 (0.45–0.94) | 12 | 19
Vertebral fractures , | 0.64 (0.44–0.93) | 11 | 18
Lower arm/wrist fractures, | 0.58 (0.47-0.72) | 35 | 59
Total fractures, | 0.71 (0.64–0.8) | 144 | 197
Death due to other causes [Results are based on an average follow-up of 6.8 years.] , [All deaths, except from breast or colorectal cancer, definite or probable CHD, PE or cerebrovascular disease.] | 1.08 (0.88-1.32) | 53 | 50
Overall Mortality, | 1.04 (0.88-1.22) | 79 | 75
Global Index [A subset of the events was combined in a "global index," defined as the earliest occurrence of CHD events, invasive breast cancer, stroke, pulmonary embolism, colorectal cancer, hip fracture, or death due to other causes.] | 1.02 (0.92-1.13) | 206 | 201

For those outcomes included in the WHI "global index" that reached statistical significance, the absolute excess risk per 10,000 women-years in the group treated with CE-alone was 12 more strokes, while the absolute risk reduction per 10,000 women-years was 7 fewer hip fractures.^9 The absolute excess risk of events included in the "global index" was a non-significant 5 events per 10,000 women-years. There was no difference between the groups in terms of all-cause mortality.

No overall difference for primary CHD events (nonfatal MI, silent MI and CHD death) and invasive breast cancer incidence in women receiving CE-alone compared with placebo was reported in final centrally adjudicated results from the estrogen-alone substudy, after an average follow-up of 7.1 years.

Centrally adjudicated results for stroke events from the estrogen-alone substudy, after an average follow-up of 7.1 years, reported no significant difference in distribution of stroke subtype or severity, including fatal strokes, in women receiving CE-alone compared to placebo. Estrogen-alone increased the risk for ischemic stroke, and this excess risk was present in all subgroups of women examined.^10

Timing of the initiation of estrogen therapy relative to the start of menopause may affect the overall risk benefit profile. The WHI estrogen-alone substudy stratified by age showed in women 50 to 59 years of age, a non-significant trend toward reduced risk for CHD [HR 0.63 (95 percent CI 0.36-1.09)] and overall mortality [HR 0.71 (95 percent CT 0.46-1.11)].

14.5 Women's Health Initiative Memory Study

The WHIMS estrogen plus progestin ancillary study of WHI enrolled 4,532 predominantly healthy postmenopausal women 65 years of age and older (47 percent were 65 to 69 years of age, 35 percent were 70 to 74 years of age, and 18 percent were 75 years of age and older) to evaluate the effects of daily CE (0.625 mg) plus MPA (2.5 mg) on the incidence of probable dementia (primary outcome) compared to placebo.

After an average follow-up of 4 years, the relative risk of probable dementia for CE plus MPA versus placebo was 2.05 (95 percent CI 1.21-3.48). The absolute risk of probable dementia for CE plus MPA was 45 versus 22 cases per 10,000 women-years. Probable dementia as defined in this study included Alzheimer's disease (AD, vascular dementia (VaD) and mixed type (having features of both AD and VaD). The most common classification of probable dementia in the treatment group and the placebo group was AD. Since the ancillary study was conducted in women 65 to 79 years of age, it is unknown whether these findings apply to younger postmenopausal women [see Warnings and Precautions (5.4), and Use in Specific Populations (8.5)].

The WHIMS estrogen-alone ancillary study of WHI enrolled 2,947 predominantly healthy hysterectomized postmenopausal women 65 to 79 years of age and older (45 percent were age 65 to 69 years of age, 36 percent were 70 to 74 years of age, and 19 percent were 75 years of age and older) to evaluate the effects of daily CE (0.625 mg) on the incidence of probable dementia (primary outcome) compared to placebo.

After an average follow-up of 5.2 years, the relative risk of probable dementia for CE-alone versus placebo was 1.49 (95 percent CI, 0.83 - 2.66). The absolute risk of probable dementia for CE-alone versus placebo was 37 versus 25 cases per 10,000 women-years. Probable dementia as defined in this study included AD, VaD, and mixed type (having features of both AD and VaD). The most common classification of probable dementia in the treatment group and placebo group was AD. Since the ancillary study was conducted in women 65 to 79 years of age, it is unknown whether these findings apply to younger postmenopausal women [see Warnings and Precautions (5.4) and Use in Specific Populations (8.5)].

When data from the two populations were pooled as planned in the WHIMS protocol, the reported overall RR for probable dementia was 1.76 (95 percent CI 1.19-2.60). Differences between groups became apparent in the first year of treatment. It is unknown whether these findings apply to younger postmenopausal women [see Warnings and Precautions (5.4), and Use in Specific Populations (8.5)].

15 REFERENCES

1. Rossouw JE, et al. Postmenopausal Hormone Therapy and Risk of Cardiovascular Disease by Age and Years Since Menopause. JAMA. 2007;297:1465-1477.
2. Hsia J, et al. Conjugated Equine Estrogens and Coronary Heart Disease. Arch Int Med. 2006;166:357-365.
3. Cushman M, et al. Estrogen Plus Progestin and Risk of Venous Thrombosis. JAMA. 2004;292:1573-1580
4. Curb JD, et al. Venous Thrombosis and Conjugated Equine Estrogen in Women Without a Uterus. Arch Int Med. 2006;166:772-780.
5. Chlebowski RT, et al. Influence of Estrogen Plus Progestin on Breast Cancer and Mammography in Healthy Postmenopausal Women. JAMA. 2003;289:3234-3253.
6. Stefanick ML, et al. Effects of Conjugated Equine Estrogens on Breast Cancer and Mammography Screening in Postmenopausal Women With Hysterectomy. JAMA. 2006;295:1647-1657.
7. Anderson GL, et al. Effects of Estrogen Plus Progestin on Gynecologic Cancers and Associated Diagnostic Procedures. JAMA. 2003;290:1739-1748.
8. Shumaker SA, et al. Conjugated Equine Estrogens and Incidence of Probable Dementia and Mild Cognitive Impairment in Postmenopausal Women. JAMA. 2004;291:2947-2958.
9. Jackson RD, et al. Effects of Conjugated Equine Estrogen on Risk of Fractures and BMD in Postmenopausal Women With Hysterectomy: Results From the Women's Health Initiative Randomized Trial. J Bone Miner Res. 2006;21:817-828.
10. Hendrix SL, et al. Effects of Conjugated Equine Estrogen on Stroke in the Women's Health Initiative. Circulation. 2006;113:2425-2434.

16 HOW SUPPLIED/STORAGE AND HANDLING

16.1 How Supplied

Angeliq is supplied in packages of three blister packs:

Angeliq 0.25 mg DRSP/0.5 mg E2

Angeliq 0.25 mg DRSP/0.5 mg E2 tablets are available as round, biconvex yellow film-coated tablets embossed with "EL" inside a hexagon.

3 blisters of 28 tablets | NDC 50419-482-03

Angeliq 0.5 mg DRSP/1 mg E2

Angeliq 0.5 mg DRSP/1 mg E2 tablets are available as round, biconvex pink film-coated tablets embossed with "CK" inside a hexagon.

3 blisters of 28 tablets | NDC 50419-483-03

16.2 Storage and Handling

Store at 20° to 25° C (68° to 77° F); excursions permitted to 15°–30° C (59°–86° F) [see USP Controlled Room Temperature].

17 PATIENT COUNSELING INFORMATION

Advise patients to read the FDA-Approved patient labeling (Patient Information).

Abnormal Vaginal Bleeding

Inform postmenopausal women to report any vaginal bleeding to their healthcare provider as soon as possible [see Warning and Precautions (5.3)].

Possible Serious Adverse Reactions with Estrogen Plus Progestogen Therapy

Inform postmenopausal women of possible serious adverse reactions of estrogen plus progestogen therapy including cardiovascular disorders, malignant neoplasms, and probable dementia [see Warning and Precautions (5.1, 5.3, 5.4)].

Possible Common Adverse Reactions with Estrogen Plus Progestogen Therapy

Inform postmenopausal women of possible less serious but common adverse reactions of estrogen plus progestogen therapy such as headache, breast pain and tenderness, nausea and vomiting [see Adverse Reactions (6)].

PATIENT INFORMATION
Angeliq® (an"ju–le–k')
(drospirenone and estradiol)
Tablets

Read this Patient Information before you start using Angeliq and read what you get each time you get a refill your Angeliq prescription. There may be new information. This information does not take the place of talking to your healthcare provider about your menopausal symptoms or your treatment.

What is the most important information I should know about Angeliq (a combination of estrogen and progestogen)?

- Do not use estrogens with or without progestogens to prevent heart disease, heart attacks, strokes, or dementia (declines of brain function).
- Using estrogens with progestogens may increase your chances of getting heart attacks, strokes, breast cancer, or blood clots.
- Using estrogens with progestogen may increase your chance of getting dementia, based on a study of women 65 years of age and older
- Using estrogen-alone may increase your chance of getting cancer of the uterus (womb).
- Do not use estrogen-alone to prevent heart disease, heart attacks, strokes, or dementia (decline in brain function).
- Using estrogen-alone may increase your chances of getting strokes or blood clots
- Using estrogen-alone may increase your chance of getting dementia, based on a study of women 65 years of age and older
- Only one estrogen with progestogen product and dose have been shown to increase your chances of getting heart attacks, strokes, breast cancer, and dementia. Only one estrogen-alone product and dose have been shown to increase your chances of getting strokes, blood clots, and dementia.
  Because other products and doses have not been studied in the same way, it is not known how the use of Angeliq will affect your chances of these conditions. You and your healthcare provider should talk regularly about whether you still need treatment with Angeliq.

What is Angeliq?

Angeliq is a prescription medicine that contains two kinds of hormones, an estrogen and a progestogen.

- Angeliq 0.25 mg drospirenone (DRSP)/0.5 mg estradiol (E2) and Angeliq 0.5 mg DRSP/1 mg E2 are both used after menopause to reduce moderate to severe hot flashes.
  Estrogens are hormones made by a woman's ovaries. The ovaries normally stop making estrogens when a woman is between 45 to 55 years old. This drop in body estrogen levels causes the "change of life" or menopause (the end of monthly menstrual periods). Sometimes, both ovaries are removed during an operation before natural menopause takes place. The sudden drop in estrogen levels causes "surgical menopause."
  When the estrogen levels begin dropping, some women develop very uncomfortable symptoms, such as feelings of warmth in the face, neck, and chest, or sudden intense feelings of heat and sweating ("hot flashes" or "hot flushes"). In some women, the symptoms are mild, and they will not need to use estrogens. In other women, symptoms can be more severe. You and your healthcare provider should talk regularly about whether you still need treatment with Angeliq.
- Angeliq 0.5 mg drospirenone (DRSP)/1 mg estradiol (E2) is used after menopause to treat menopausal changes in or around the vagina. You and your healthcare provider should talk regularly about whether you still need treatment with Angeliq to control these problems. If you use Angeliq only to treat your menopausal changes in and around your vagina, talk with your healthcare provider about whether a topical vaginal product would be better for you.

Who should not use Angeliq?

Do not start using Angeliq if you:

- have had your uterus (womb) removed (hysterectomy). Angeliq contains a progestogen to decrease the chances of getting cancer of the uterus. If you do not have a uterus, you do not need a progestogen and you should not use Angeliq.
- have unusual vaginal bleeding. Vaginal bleeding after menopause may be a warning sign of cancer of the uterus (womb). Your healthcare provider should check any unusual vaginal bleeding to find out the cause.
- Have been diagnosed with a bleeding disorder.
- currently have or have had certain cancers. Estrogens may increase the chances of getting certain types of cancers, including cancer of the breast or uterus. If you have or had cancer, talk with your healthcare provider about whether you should use Angeliq.
- currently have or have had blood clots.
- Had a stroke or heart attack
- have kidney disease, liver disease, or disease of your adrenal glands. Angeliq contains drospirenone which may increase the potassium level in your blood. Liver, kidney, or adrenal gland disease may also increase the potassium level in your blood.
- are allergic to Angeliq or any of its ingredients. See the list of ingredients in Angeliq at the end of this leaflet.

Before you use Angeliq, tell your healthcare provider if you:

- have or have had problems with your adrenal glands
- have high levels of fat in your blood (triglycerides)
- have any other medical conditions that may become worse while you are using Angeliq
  Your healthcare provider may need to check you more carefully if you have certain conditions, such as:
  - asthma (wheezing)
  - epilepsy (seizures)
  - diabetes
  - migraine
  - endometriosis
  - lupus
  - have high potassium levels in your blood
  - hypertension (high blood pressure)
  - problems with your heart, liver, thyroid or kidneys
  - benign breast disease
  - have high calcium in your blood
  - have low sodium levels in your blood
- are pregnant or think you may be pregnant
  Angeliq is not for pregnant women.
- are going to have surgery or will be on bed rest. Your healthcare provider will let you know if you need to stop using Angeliq.
- are breastfeeding
  The hormones in Angeliq can pass into your milk.
  Tell your healthcare provider about all the medicines you take, including prescription and over-the-counter medicines, vitamins, and herbal supplements. Some medicines may affect how Angeliq works. Some other medicines and food products may increase or decrease the concentrations of the hormones in Angeliq in the blood. Angeliq may also affect how your other medicines work. Angeliq may increase the potassium level in your blood and some medicines may also increase potassium level. In some situations, your healthcare provider may recommend testing your blood for potassium level.
  Keep a list of your medicines and show it to your doctor and pharmacist when you get a new medicine.

How should I use Angeliq?

- Take one Angeliq tablet at the same time each day.
- Take Angeliq tablets whole. Do not break, crush, dissolve, or chew Angeliq tablets before swallowing. If you cannot swallow Angeliq tablets whole, tell your healthcare provider. You may need a different medicine.
- If you miss a dose of Angeliq, take it as soon as possible.
- If more than 24 hours have passed since you missed a dose of Angeliq, you should not take the missed dose.
- Estrogens should be used at the lowest dose possible for your treatment only as long as needed. You and your healthcare provider should talk regularly (for example, every 3 to 6 months) about whether you still need treatment with Angeliq.

What are the possible side effects of Angeliq?

Side effects are grouped by how serious they are and how often they happen when you are treated.

Serious but less common side effects include:

- Heart attack
- Stroke
- Blood clots
- High potassium levels in your blood (hyperkalemia)
- Cancer of the lining of the uterus (womb)
- Breast cancer
- Cancer of the ovary
- Dementia
- Enlargement of benign tumors of the uterus ("fibroids")

- Gallbladder disease
- High or low blood calcium
- High blood pressure
- High levels of fat (triglycerides) in your blood
- Liver problems
- Changes in your thyroid hormone levels
- Fluid retention
- Worsening of swelling of face and tongue (angioedema) in women with a history of angioedema

Call your healthcare provider right away if you have any of the following warning signs or any other unusual symptoms that concern you:

- New breast lumps
- Changes in vision or speech
- Unusual vaginal bleeding
- Sudden new severe headaches

- Severe pains in your chest or legs with or without shortness of breath, weakness and fatigue

Common side effects of Angeliq include:

- Headache
- Breast pain
- Irregular vaginal bleeding or spotting
- Stomach or abdominal pain
- Nausea

- Diarrhea
- Vaginal yeast infection
- Fluid Retention
- Moodiness

These are not all the possible side effects of Angeliq. For more information, ask your healthcare provider or pharmacist about side effects.

You may report side effects to Bayer HealthCare Pharmaceuticals at 1-888-842-2937 or to FDA at 1-800-FDA-1088.

How should I store Angeliq?

Store Angeliq at room temperature between 68˚F to 77˚F (20˚C to 25˚C).

Keep Angeliq and all medicines out of the reach of children.

What can I do to lower my chances of a serious side effect with Angeliq?

- Talk with your healthcare provider regularly about whether you should continue using Angeliq.
- If you have a uterus, talk with your healthcare provider about whether Angeliq is right for you.
- In general, the addition of a progestogen is recommended for a women with a uterus to reduce the chances of getting cancer of the uterus (womb).
- See your healthcare provider right away if you get vaginal bleeding while using Angeliq.
- Have a pelvic exam, breast exam and mammogram (breast X-ray) every year unless your healthcare provider tells you something else. If members of your family have had breast cancer or if you have ever had breast lumps or an abnormal mammogram, you may need to have breast exams more often.
- If you have high blood pressure, high cholesterol (fat in the blood), diabetes, are overweight, or if you use tobacco, you may have higher chances for getting heart disease. Ask your healthcare provider for ways to lower your chances for getting heart disease.

General information about the safe and effective use of Angeliq.

Medicines are sometimes prescribed for purposes other than those listed in a Patient Information leaflet. Do not use Angeliq for conditions for which it was not prescribed. Do not give Angeliq to other people, even if they have the same symptoms you have. It may harm them.

You can ask your pharmacist or healthcare provider for information about Angeliq that is written for health professionals.

For more information, go to www.angeliq-us.com by or calling our toll free number (1-888-842-2937).

What are the ingredients in Angeliq?

Active ingredients: drospirenone (a progestin) and estradiol.

Inactive ingredients 0.5 mg DRSP/1 mg E2 tablets: lactose monohydrate NF, corn starch NF, pregelatinized starch NF, povidone 25000 USP, magnesium stearate NF, hydroxylpropylmethyl cellulose USP, macrogol 6000 NF, talc USP, titanium dioxide USP, and ferric oxide pigment NF.

Inactive ingredients in 0.25 mg DRSP/0.5 mg E2 tablets: lactose monohydrate NF, corn starch NF, pregelatinized starch NF, povidone 25000 USP, magnesium stearate NF, hydroxylpropylmethyl cellulose USP, macrogol 6000 NF, talc USP, titanium dioxide USP, and yellow ferric oxide pigment NF.

This Patient Information has been approved by the U.S. Food and Drug Administration.

Manufactured for:
Bayer HealthCare Pharmaceuticals Inc.
Whippany, NJ 07981

©2015 Bayer HealthCare Pharmaceuticals Inc
All rights reserved.
October 2023

PACKAGE LABEL

Angeliq 0.5 mg Trade Carton

NDC 50419-483-01

1 Unit

Rx Only

Angeliq® Tablets

(Drospirenone and Estradiol)

0.5 mg/1 mg

— 0.5 mg/1 mg

— 28 tablets

— oral

Angeliq 0.25 mg Trade Carton

NDC 50419-482-01

1 Unit

Rx Only

Angeliq® Tablets

(Drospirenone and Estradiol)

0.25 mg/0.5 mg

— 0.25 mg/0.5 mg

— 28 tablets

— oral